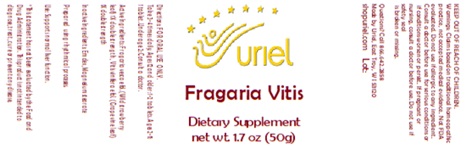 DRUG LABEL: Fragaria Vitis
NDC: 48951-4199 | Form: TABLET
Manufacturer: Uriel Pharmacy, Inc
Category: homeopathic | Type: HUMAN OTC DRUG LABEL
Date: 20250904

ACTIVE INGREDIENTS: FRAGARIA VESCA WHOLE 1 [hp_X]/1 1; VITIS VINIFERA LEAF 1 [hp_X]/1 1
INACTIVE INGREDIENTS: DEXTRATES; MAGNESIUM STEARATE

Fragaria Vitis Dietary Supplement net wt. 1.7 oz (50g)

INDICATIONS AND USAGE

Directions: FOR ORAL USE ONLY.

DOSAGE AND ADMINISTRATION

Take 3-4 times daily. Ages 12 and older: 1-2 tablets.

Ages 2-11: 1 tablet. Under age 2: Consult a doctor.

ACTIVE INGREDIENT

Active Ingredients: Fragaria vesca e fol. (Wild strawberry leaf) 1X double strength, Vitis vinifera e fol. (Grape vine leaf) 1X double strength

Inactive Ingredients: Emdex, Magnesium stearate

Prepared using rhythmical processes.

PURPOSE

Use: Supports normal liver function.

KEEP OUT OF REACH OF CHILDREN.

WARNINGS

Warnings: Claims based on traditional homeopathic practice, not accepted medical evidence.
Not FDA evaluated. Do not use if allergic to any ingredient. Consult a doctor before use for
serious conditions or if conditions worsen or persist. If pregnant or nursing, consult a
doctor before use. Do not use if safety seal is broken or missing.

*This statement has not been evaluated by the Food and Drug Administration. This product is not intended to diagnose, treat, cure or prevent any disease.

Questions? Call 866.642.2858
Made by Uriel, East Troy, WI 53120
shopuriel.com Lot: